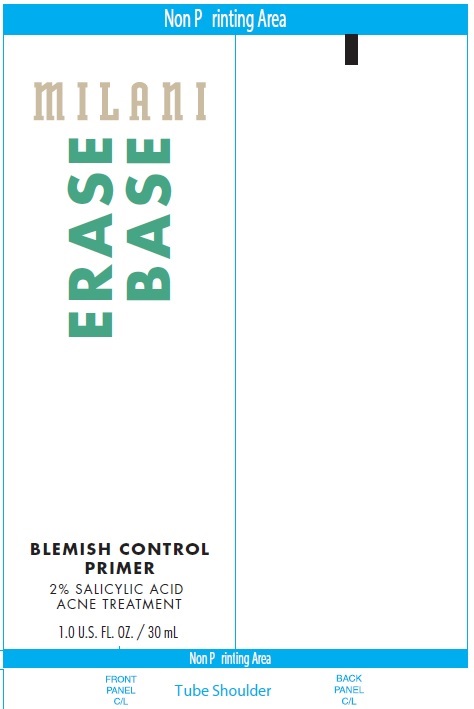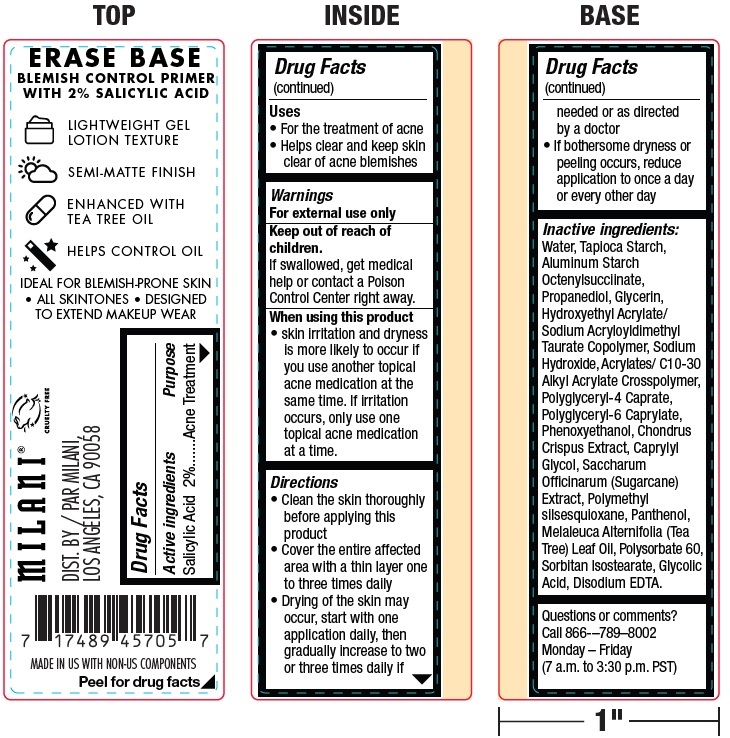 DRUG LABEL: Milani Erase Base Blemish Control Primer
NDC: 68577-103 | Form: GEL
Manufacturer: Cosmax Usa, Corporation
Category: otc | Type: HUMAN OTC DRUG LABEL
Date: 20241226

ACTIVE INGREDIENTS: SALICYLIC ACID 20 mg/1 mL
INACTIVE INGREDIENTS: WATER; STARCH, TAPIOCA; PROPANEDIOL; GLYCERIN; SODIUM HYDROXIDE; POLYGLYCERYL-4 CAPRATE; POLYGLYCERYL-6 CAPRYLATE; PHENOXYETHANOL; CHONDRUS CRISPUS CARRAGEENAN; CAPRYLYL GLYCOL; SUGARCANE; POLYMETHYLSILSESQUIOXANE (4.5 MICRONS); PANTHENOL; TEA TREE OIL; POLYSORBATE 60; SORBITAN ISOSTEARATE; GLYCOLIC ACID; EDETATE DISODIUM ANHYDROUS

Milani Erase Base Blemish Control Primer with 2% Salicylic Acid

Active ingredients

Salicylic Acid 2%

Purpose

Acne Treatment

Uses

• For the treatment of acne
• Helps clear and keep skin clear of acne blemishes

Warnings

For external use only

Keep out of reach of children.

If swallowed, get medical help or contact a Poison Control Center right away.

When using this product

• skin irritation and dryness is more likely to occur if you use another topical acne medication at the same time. If irritation occurs, only use one topical acne medication at a time.

Directions

• Clean the skin thoroughly before applying this product
• Cover the entire affected area with a thin layer one to three times daily
• Drying of the skin may occur, start with one application daily, then gradually increase to two or three times daily if needed or as directed by a doctor
• If bothersome dryness or peeling occurs, reduce application to once a day or every other day

Inactive ingredients:

Water, Tapioca Starch, Aluminum Starch Octenylsucciinate, Propanediol, Glycerin, Hydroxyethyl Acrylate/ Sodium Acryloyldimethyl Taurate Copolymer, Sodium Hydroxide, Acrylates/ C10-30 Alkyl Acrylate Crosspolymer, Polyglyceryl-4 Caprate, Polyglyceryl-6 Caprylate, Phenoxyethanol, Chondrus Crispus Extract, Caprylyl Glycol, Saccharum Officinarum (Sugarcane) Extract, Polymethyl silsesquioxane, Panthenol, Melaleuca Alternifolia (Tea Tree) Leaf Oil, Polysorbate 60, Sorbitan Isostearate, Glycolic Acid, Disodium EDTA.

Questions or comments?

Call 866-–789–8002 Monday – Friday (7 a.m. to 3:30 p.m. PST)